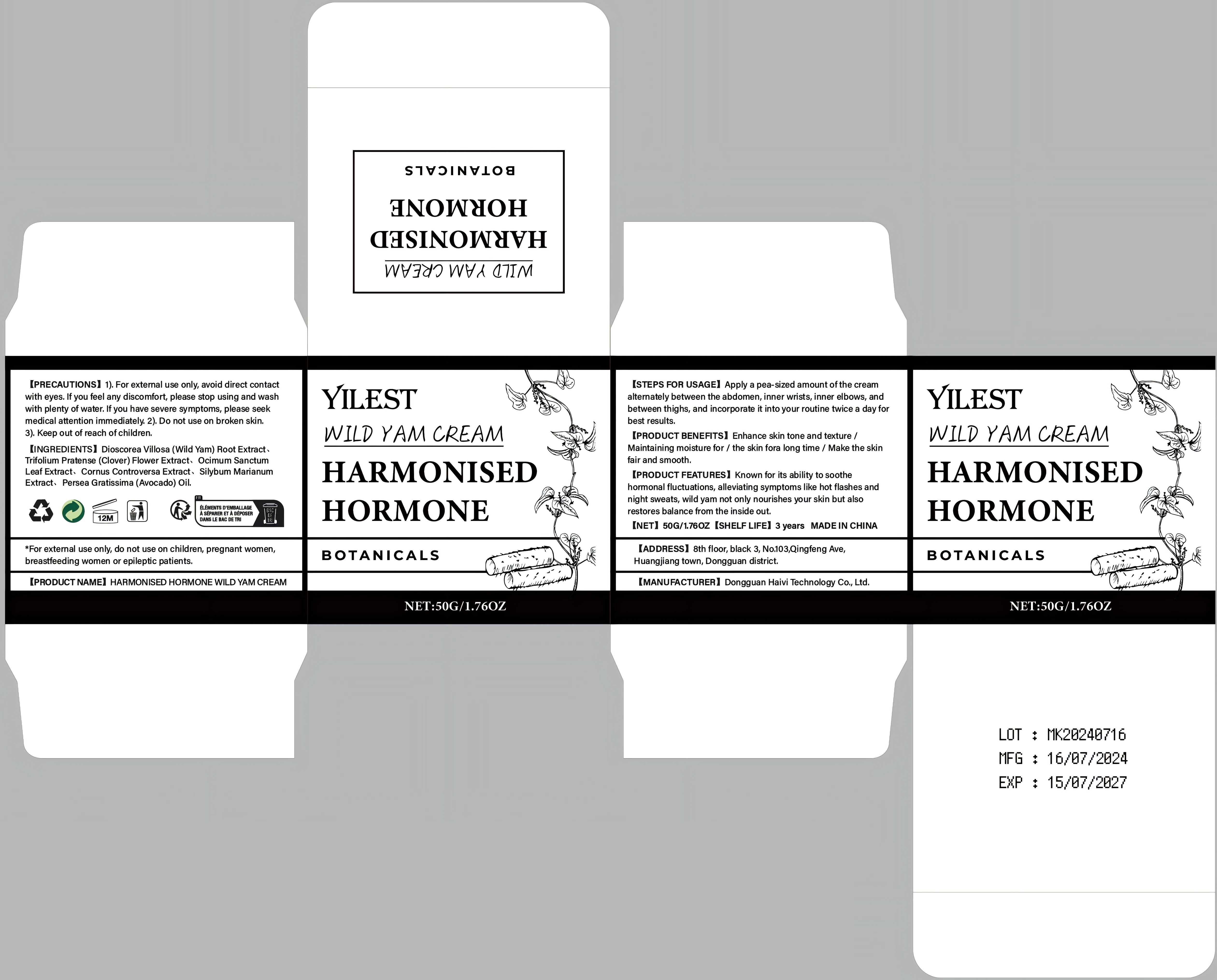 DRUG LABEL: HARMONISED HORMONE WILD YAM Cream
NDC: 84732-080 | Form: CREAM
Manufacturer: Dongguan Haiyi Technology Co.,Ltd.
Category: otc | Type: HUMAN OTC DRUG LABEL
Date: 20241101

ACTIVE INGREDIENTS: TRIFOLIUM PRATENSE FLOWER 1 mg/50 g
INACTIVE INGREDIENTS: DIOSCOREA VILLOSA (WILD YAM) ROOT EXTRACT; CORNUS CONTROVERSA LEAF; HOLY BASIL LEAF; MILK THISTLE; AVOCADO OIL

Active ingredient

Trifolium Pratense (Clover) Flower Extract

Inactive ingredient

Dioscorea Villosa (Wild Yam) Root Extract、Ocimum Sanctum Leaf Extract、Cornus Controversa Extract、Silybum Marianum Extract、Persea Gratissima (Avocado) Oil.

Purpose section

Known for its ability to soothe hormonal fluctuations, alleviating symptoms like hot flashes andnight sweats, wild yam not only nourishes your skin but alsorestores balance from the inside out.

Warning

1).For extemal use only, avoid direct contactwith eyes, lf you feel any discomfort, please stop using and washwith plenty of water, lfyou have severe symptoms, please seekmedical attention immediately

2). Do not use on broken skin.

3). Keep out of reach of children.

stop use

1).For extemal use only, avoid direct contact with eyes, lf you feel any discomfort, please stop using and washwith plenty of water, lf you have severe symptoms, please seek medical attention immediately

not use

Not suitable for use by children, pregnantor breast feeding people.

OUT OF CHILDREN

KEEP THE PRODUCT OUT OF REACH OF CHILDREN to

HOW TO USE

Apply a pea-sized amount ofthe cream altemately between the abdomen,inner wrists, inner elbows, and between thighs, and incorporate it into your routine twice a day forbest results.

Dosage

it into your routine twice a day for best results.